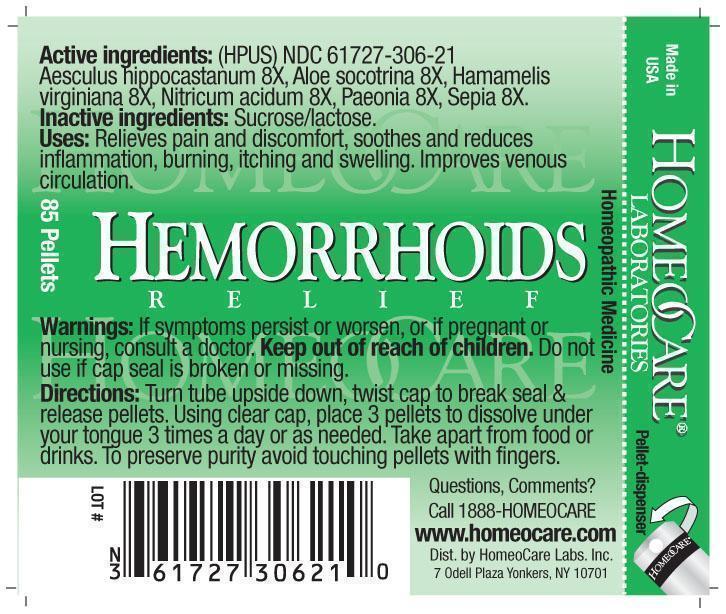 DRUG LABEL: Hemorrhoids Relief
NDC: 61727-306 | Form: PELLET
Manufacturer: Homeocare Laboratories
Category: homeopathic | Type: HUMAN OTC DRUG LABEL
Date: 20260115

ACTIVE INGREDIENTS: HORSE CHESTNUT 8 [hp_X]/4 g; ALOE 8 [hp_X]/4 g; HAMAMELIS VIRGINIANA ROOT BARK/STEM BARK 8 [hp_X]/4 g; NITRIC ACID 8 [hp_X]/4 g; PAEONIA OFFICINALIS ROOT 8 [hp_X]/4 g; SEPIA OFFICINALIS JUICE 8 [hp_X]/4 g
INACTIVE INGREDIENTS: SUCROSE; LACTOSE

Hemorrhoids Relief

Active ingredients:

Aesculus hippocastanum 8X, Aloe socotrina 8X, Hamamelis virginiana 8X, Nitricum acidum 8X, Paeonia 8X, Sepia 8X.

Purpose:

Relieves pain and discomfort, soothes and reduces inflammation, burning, itching and swelling. Improves venous circulation.

Keep out of reach of children.

Indications & Usage:

Turn tube upside down, twist cap to break seal & release pellets. Using clear cap, place 3 pellets to dissolve under your tongue 3 times a day or as needed. Take apart from food or drinks. To preserve purity avoid touching pellets with fingers.

Warnings:

If symptoms persist or worsen, or if pregnant or nursing, consult a doctor. Keep out of reach of children. Do not use if cap seal is broken or missing.

Inactive ingredients:

Sucrose/lactose.

Dosage & Administration:

Turn tube upside down, twist cap to break seal & release pellets. Using clear cap, place 3 pellets to dissolve under your tongue 3 times a day or as needed. Take apart from food or drinks.To preserve purity avoid touching pellets with fingers.

Hemorrhoids Relief

Homeopathic Medicine

85 Pellets
hcl_label_hhoids 2012.jpg